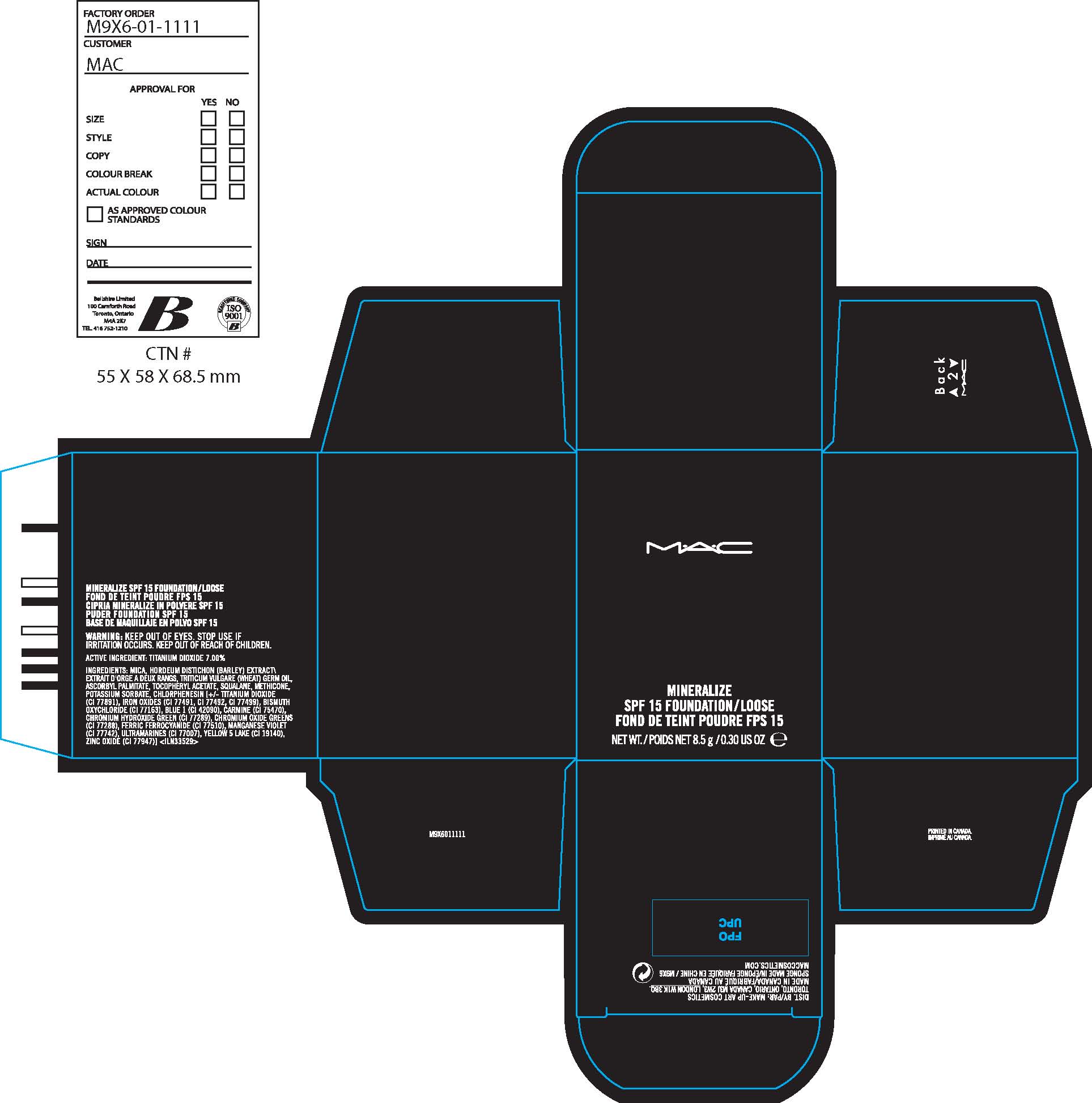 DRUG LABEL: MINERALIZE
NDC: 40046-0031 | Form: POWDER
Manufacturer: MAKEUP ART COSMETICS
Category: otc | Type: HUMAN OTC DRUG LABEL
Date: 20110912

ACTIVE INGREDIENTS: TITANIUM DIOXIDE 7.0 g/100 g
INACTIVE INGREDIENTS: MICA; BARLEY BRAN; WHEAT GERM OIL; ASCORBYL PALMITATE; ALPHA-TOCOPHEROL ACETATE; SQUALANE; POTASSIUM SORBATE; CHLORPHENESIN; FERRIC OXIDE RED; BISMUTH OXYCHLORIDE; FD&C BLUE NO. 1; COCHINEAL; CHROMIC OXIDE; FD&C YELLOW NO. 5; ALUMINUM OXIDE

ACTIVE INGREDIENT: TITANIUM DIOXIDE 7.0%

INACTIVE INGREDIENT

INACTIVE INGREDIENTS: MICA [] HORDEUM DISTICHON (BARLEY) EXTRACT\EXTRAIT D'ORGE A DEUX RANGS [] TRITICUM VULGARE (WHEAT) GERM OIL [] ASCORBYL PALMITATE [] TOCOPHERYL ACETATE [] SQUALANE [] METHICONE [] POTASSIUM SORBATE [] CHLORPHENESIN [] [+/- TITANIUM DIOXIDE (CI 77891) [] IRON OXIDES (CI 77491, CI 77492, CI 77499) [] BISMUTH OXYCHLORIDE (CI 77163) [] BLUE 1 (CI 42090) [] CARMINE (CI 75470) [] CHROMIUM HYDROXIDE GREEN (CI 77289) [] CHROMIUM OXIDE GREENS (CI 77288) [] FERRIC FERROCYANIDE (CI 77510) [] YELLOW 5 LAKE (CI 19140) [] ZINC OXIDE (CI 77947)

WARNINGS

WARNING: KEEP OUT OF EYES. DISCONTINUE USE IF IRRITATION DEVELOPS. KEEP OUT OF REACH OF CHILDREN.

PACKAGE LABEL

PRINCIPAL DISPLAY PANEL:

MAC

MINERALIZE

SPF 15 FOUNDATION

LOOSE

8.5 g/ 0.30 US oz
makeup art cosmetics distr.
toronto, CANADA M3J 2W3